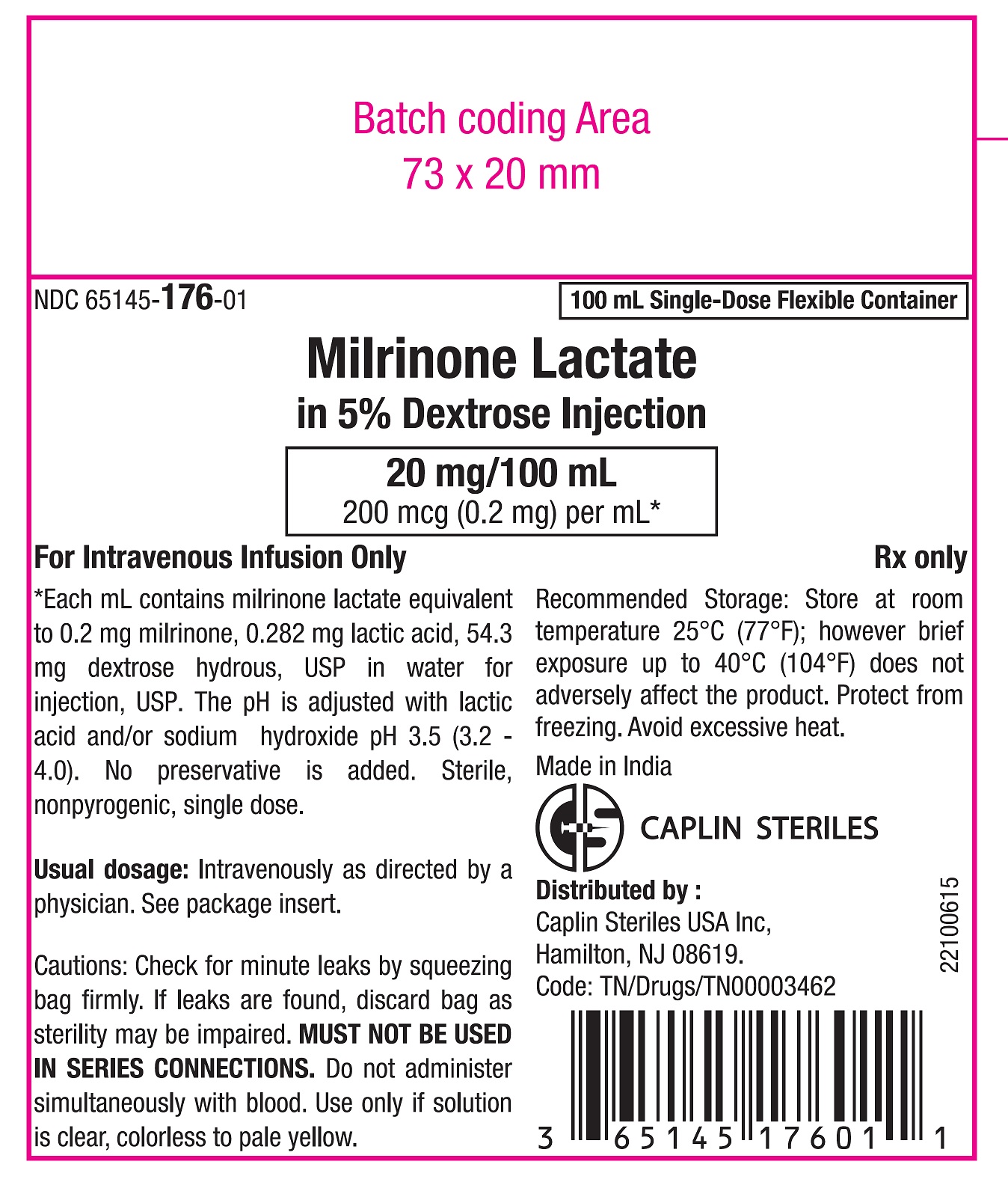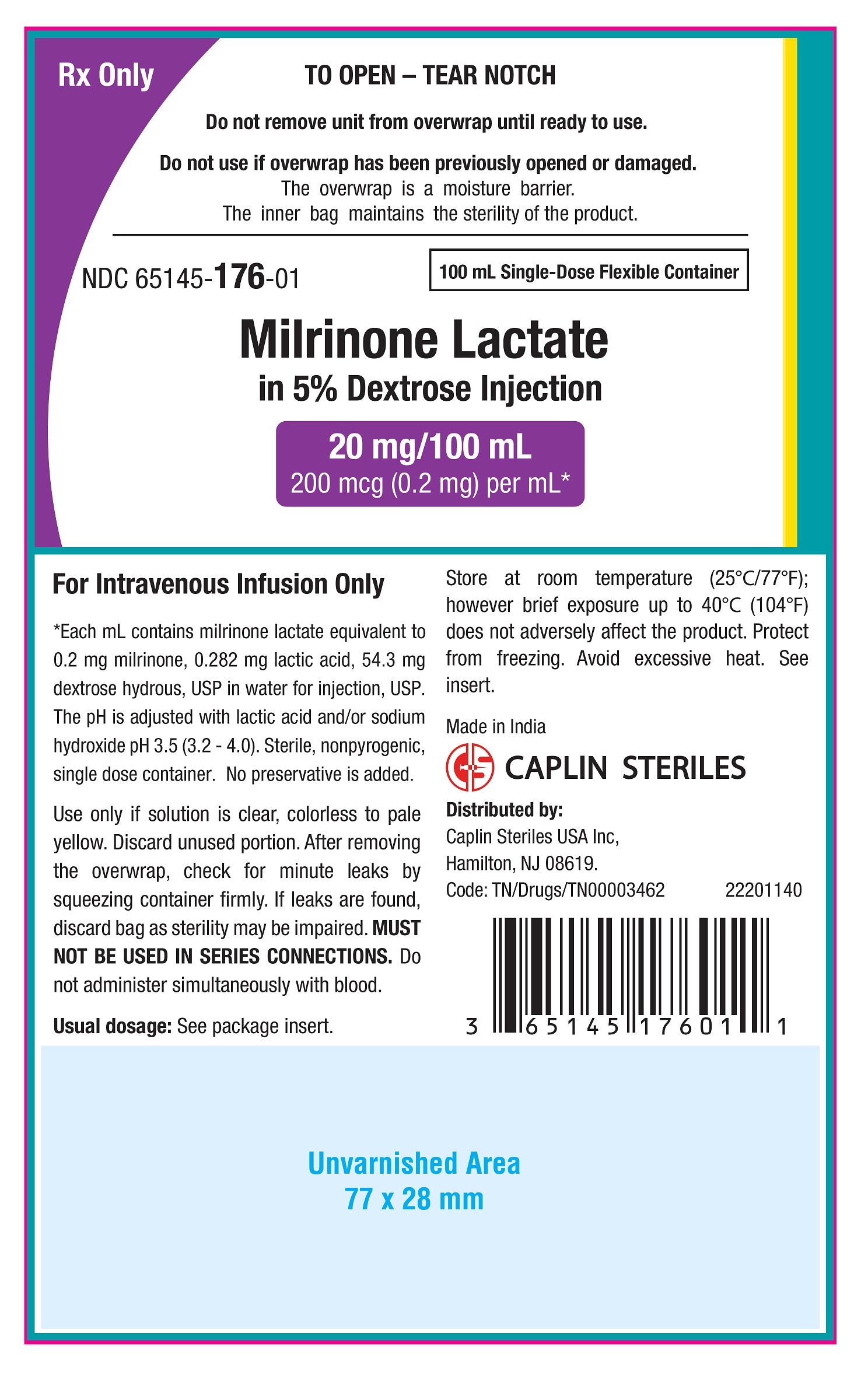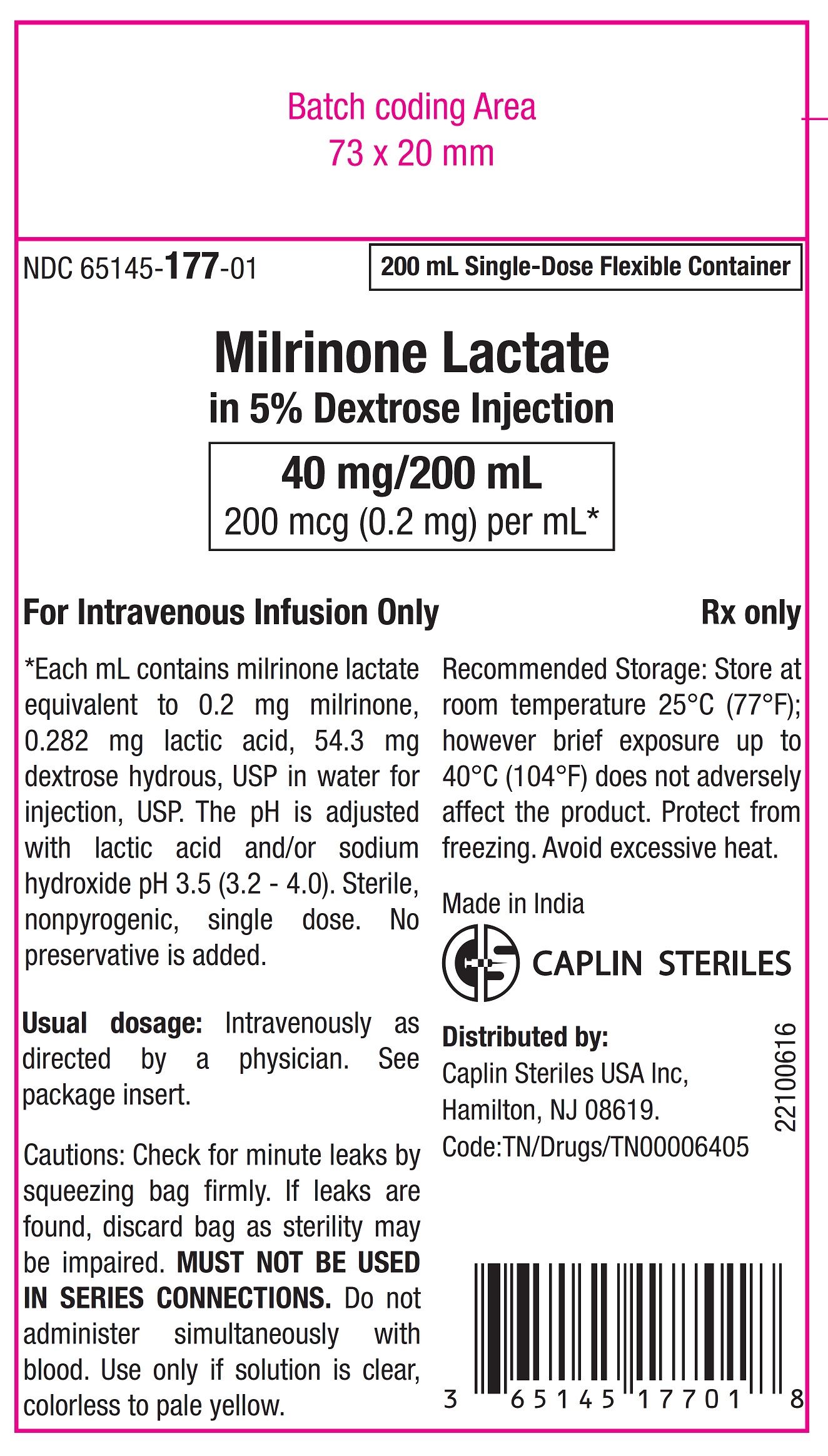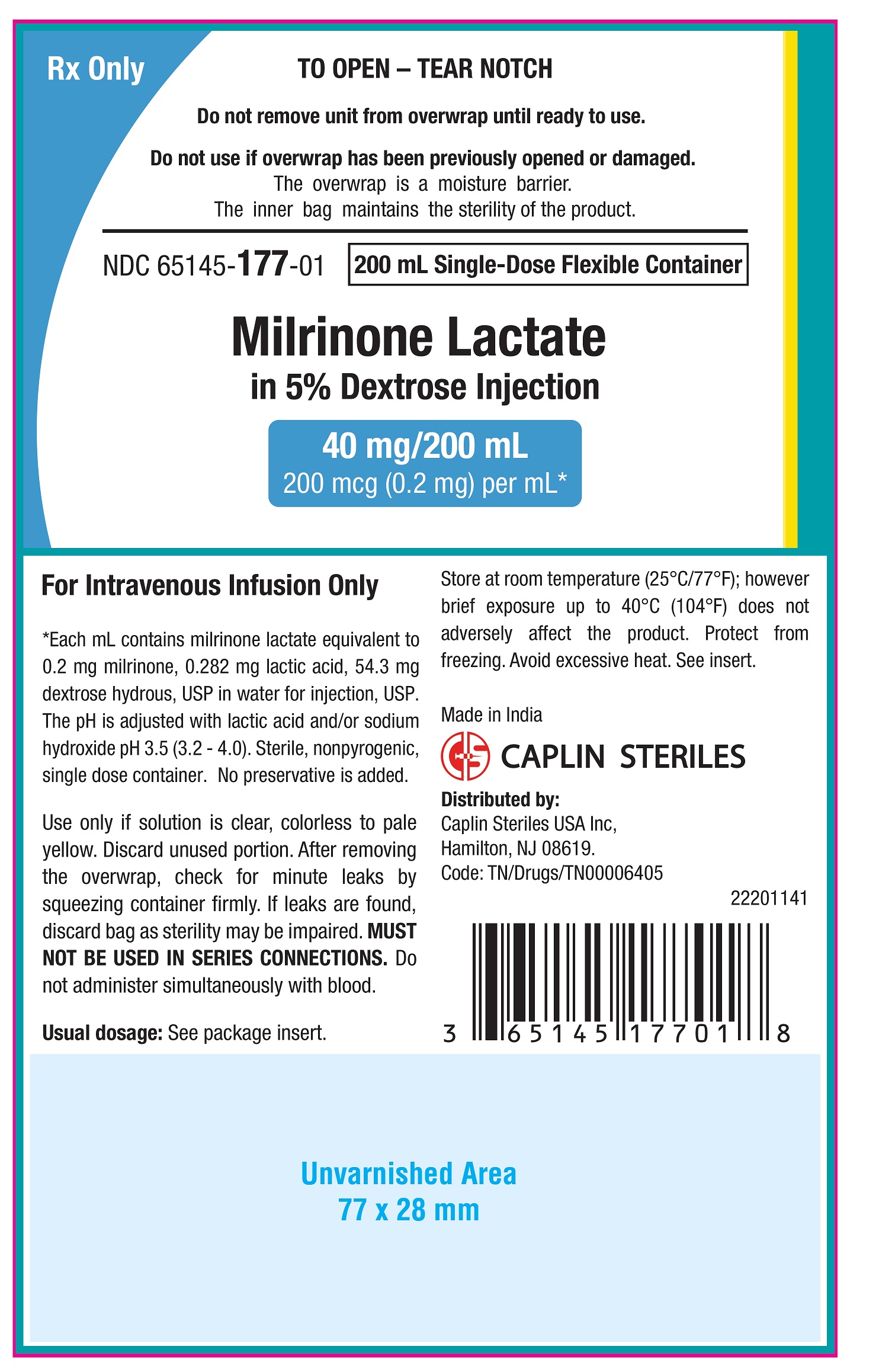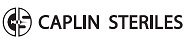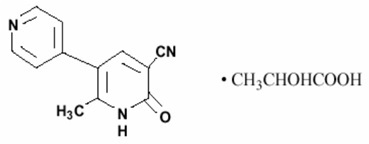 DRUG LABEL: Milrinone Lactate in 5% Dextrose
NDC: 65145-176 | Form: INJECTION, SOLUTION
Manufacturer: Caplin Steriles Limited
Category: prescription | Type: Human Prescription Drug Label
Date: 20250913

ACTIVE INGREDIENTS: MILRINONE LACTATE 0.2 mg/1 mL
INACTIVE INGREDIENTS: LACTIC ACID 0.282 mg/1 mL; DEXTROSE MONOHYDRATE 54.3 mg/1 mL; WATER; SODIUM HYDROXIDE

Milrinone Lactate in 5% Dextrose Injection

DESCRIPTION

Milrinone lactate is a member of a new class of bipyridine inotropic/vasodilator agents with phosphodiesterase inhibitor activity, distinct from digitalis glycosides or catecholamines. Milrinone lactate is designated chemically as 1,6- dihydro-2-methyl-6-oxo-[3,4’-bipyridine]-5-carbonitrile lactate and has the following structure:

Milrinone, USP is a white to tan crystalline compound with a molecular weight of 211.2 and a molecular formula of C12H9N3O. It is freely soluble in dimethyl sulfoxide; very slightly soluble in methanol, practically insoluble in water and in chloroform. As the lactate salt, it is stable and colorless to pale yellow in solution. Milrinone is available as sterile aqueous solutions of the lactate salt of milrinone for infusion intravenously. The Flexible containers provide two ready-to-use dilutions of milrinone in volumes of 100 mL and 200 mL of 5% Dextrose Injection. Each mL contains milrinone lactate equivalent to 200 mcg milrinone. The nominal concentration of lactic acid is 0.282 mg/mL. Each mL also contains 54.3 mg dextrose, hydrous, USP. The pH is adjusted to between 3.2 and 4.0 with lactic acid and/or sodium hydroxide. The flexible plastic container is comprised of polypropylene with a foil overwrap. Water can permeate the plastic into the overwrap, but the amount is insufficient to significantly affect the premixed solution.

CLINICAL PHARMACOLOGY

Milrinone is a positive inotrope and vasodilator, with little chronotropic activity different in structure and mode of action from either the digitalis glycosides or catecholamines.

Milrinone at relevant inotropic and vasorelaxant concentrations, is a selective inhibitor of peak III cAMP phosphodiesterase isozyme in cardiac and vascular muscle. This inhibitory action is consistent with cAMP mediated increases in intracellular ionized calcium and contractile force in cardiac muscle, as well as with cAMP dependent contractile protein phosphorylation and relaxation in vascular muscle. Additional experimental evidence also indicates that Milrinone is not a beta-adrenergic agonist nor does it inhibit sodium-potassium adenosine triphosphatase activity as do the digitalis glycosides.

Clinical studies in patients with congestive heart failure have shown that Milrinone produces dose-related and plasma drug concentration-related increases in the maximum rate of increase of left ventricular pressure. Studies in normal subjects have shown that milrinone produces increases in the slope of the left ventricular pressure-dimension relationship, indicating a direct inotropic effect of the drug. Milrinone also produces dose-related and plasma concentration-related increases in forearm blood flow in patients with congestive heart failure, indicating a direct arterial vasodilator activity of the drug.

Both the inotropic and vasodilatory effects have been observed over the therapeutic range of plasma milrinone concentrations of 100 ng/mL to 300 ng/mL.

In addition to increasing myocardial contractility, milrinone improves diastolic function as evidenced by improvements in left ventricular diastolic relaxation.

The acute administration of intravenous milrinone has also been evaluated in clinical trials in excess of 1600 patients, with chronic heart failure, heart failure associated with cardiac surgery, and heart failure associated with myocardial infarction. The total number of deaths, either on therapy or shortly thereafter (24 hours) was 15, less than 0.9%, few of which were thought to be drug-related.

PHARMACOKINETICS

Following intravenous injections of 12.5 mcg/kg to 125 mcg/kg to congestive heart failure patients, milrinone had a volume of distribution of 0.38 liters/kg, a mean terminal elimination half-life of 2.3 hours, and a clearance of 0.13 liters/kg/hr. Following intravenous infusions of 0.20 mcg/kg/min to 0.70 mcg/kg/min to congestive heart failure patients, the drug had a volume of distribution of about 0.45 liters/kg, a mean terminal elimination half-life of 2.4 hours, and a clearance of 0.14 liters/kg/hr. These pharmacokinetic parameters were not dose-dependent, and the area under the plasma concentration versus time curve following injections was significantly dose-dependent.

Milrinone has been shown (by equilibrium dialysis) to be approximately 70% bound to human plasma protein.

The primary route of excretion of milrinone in man is via the urine. The major urinary excretions of orally administered milrinone in man are milrinone (83%) and its O-glucuronide metabolite (12%). Elimination in normal subjects via the urine is rapid, with approximately 60% recovered within the first two hours following dosing and approximately 90% recovered within the first eight hours following dosing. The mean renal clearance of milrinone is approximately 0.3 liters/min, indicative of active secretion.

PHARMACODYNAMICS

In patients with heart failure due to depressed myocardial function, milrinone produced a prompt dose and plasma concentration related increase in cardiac output and decreases in pulmonary capillary wedge pressure and vascular resistance, which were accompanied by mild-to-moderate increases in heart rate. Additionally, there is no increased effect on myocardial oxygen consumption. In uncontrolled studies, hemodynamic improvement during intravenous therapy with milrinone was accompanied by clinical symptomatic improvement, but the ability of milrinone to relieve symptoms has not been evaluated in controlled clinical trials. The great majority of patients experience improvements in hemodynamic function within 5 to 15 minutes of the initiation of therapy.

In studies in congestive heart failure patients, milrinone when administered as a loading injection followed by a maintenance infusion produced significant mean initial increases in cardiac index of 25 percent, 38 percent, and 42 percent at dose regimens of 37.5 mcg/kg/0.375 mcg/kg/ min, 50 mcg/kg/0.50 mcg/kg/min, and 75 mcg/kg/0.75 mcg/kg/min, respectively. Over the same range of loading injections and maintenance infusions, pulmonary capillary wedge pressure significantly decreased by 20 percent, 23 percent, and 36 percent, respectively, while systemic vascular resistance significantly decreased by 17 percent, 21 percent, and 37 percent. Mean arterial pressure fell by up to 5 percent at the two lower dose regimens, but by 17 percent at the highest dose. Patients evaluated for 48 hours maintained improvements in hemodynamic function, with no evidence of diminished response (tachyphylaxis). A smaller number of patients have received infusions of milrinone for periods up to 72 hours without evidence of tachyphylaxis.

The duration of therapy should depend upon patient responsiveness.

Milrinone has a favorable inotropic effect in fully digitalized patients without causing signs of glycoside toxicity. Theoretically, in cases of atrial flutter/fibrillation, it is possible that milrinone may increase ventricular response rate because of its slight enhancement of AV node conduction. In these cases, digitalis should be considered prior to the institution of therapy with milrinone.

Improvement in left ventricular function in patients with ischemic heart disease has been observed. The improvement has occurred without inducing symptoms or electrocardiographic signs of myocardial ischemia.

The steady-state plasma milrinone concentrations after approximately 6 to 12 hours of unchanging maintenance infusion of 0.50 mcg/kg/min are approximately 200 ng/mL. Near maximum favorable effects of milrinone on cardiac output and pulmonary capillary wedge pressure are seen at plasma milrinone concentrations in the 150 ng/mL to 250 ng/mL range.

INDICATIONS AND USAGE

Milrinone is indicated for the short-term intravenous treatment of patients with acute decompensated heart failure. Patients receiving milrinone should be observed closely with appropriate electrocardiographic equipment. The facility for immediate treatment of potential cardiac events, which may include life threatening ventricular arrhythmias, must be available. The majority of experience with intravenous milrinone has been in patients receiving digoxin and diuretics. There is no experience in controlled trials with infusions of milrinone for periods exceeding 48 hours.

CONTRAINDICATIONS

Milrinone is contraindicated in patients who are hypersensitive to it.

Solutions containing dextrose may be contraindicated in patients with known allergy to corn or corn products.

WARNINGS

Whether given orally or by continuous or intermittent intravenous infusion, milrinone has not been shown to be safe or effective in the longer (greater than 48 hours) treatment of patients with heart failure. In a multicenter trial of 1088 patients with Class III and IV heart failure, long-term oral treatment with milrinone was associated with no improvement in symptoms and an increased risk of hospitalization and death. In this study, patients with Class IV symptoms appeared to be at particular risk of life-threatening cardiovascular reactions. There is no evidence that milrinone given by long-term continuous or intermittent infusion does not carry a similar risk.

The use of milrinone both intravenously and orally has been associated with increased frequency of ventricular arrhythmias, including nonsustained ventricular tachycardia. Long-term oral use has been associated with an increased risk of sudden death. Hence, patients receiving milrinone should be observed closely with the use of continuous electrocardiographic monitoring to allow the prompt detection and management of ventricular arrhythmias.

PRECAUTIONS

General

Milrinone should not be used in patients with severe obstructive aortic or pulmonic valvular disease in lieu of surgical relief of the obstruction. Like other inotropic agents, it may aggravate outflow tract obstruction in hypertrophic subaortic stenosis.

Supraventricular and ventricular arrhythmias have been observed in the high-risk population treated. In some patients, injections of milrinone and oral milrinone have been shown to increase ventricular ectopy, including nonsustained ventricular tachycardia. The potential for arrhythmia, present in congestive heart failure itself, may be increased by many drugs or combinations of drugs. Patients receiving milrinone should be closely monitored during infusion.

Milrinone produces a slight shortening of AV node conduction time, indicating a potential for an increased ventricular response rate in patients with atrial flutter/fibrillation which is not controlled with digitalis therapy.

During therapy with milrinone, blood pressure and heart rate should be monitored and the rate of infusion slowed or stopped in patients showing excessive decreases in blood pressure.

If prior vigorous diuretic therapy is suspected to have caused significant decreases in cardiac filling pressure, milrinone should be cautiously administered with monitoring of blood pressure, heart rate, and clinical symptomatology.

There is no experience in controlled trials with infusions of milrinone for periods exceeding 48 hours. Cases of infusion site reaction have been reported with intravenous milrinone therapy (see ADVERSE REACTIONS). Consequently, careful monitoring of the infusion site should be maintained to avoid possible extravasation.

Use in Acute Myocardial Infarction

No clinical studies have been conducted in patients in the acute phase of post myocardial infarction. Until further clinical experience with this class of drugs is gained, milrinone is not recommended in these patients.

Laboratory Tests

Fluid and electrolytes: Fluid and electrolyte changes and renal function should be carefully monitored during therapy with milrinone. Improvement in cardiac output with resultant diuresis may necessitate a reduction in the dose of diuretic. Potassium loss due to excessive diuresis may predispose digitalized patients to arrhythmias. Therefore, hypokalemia should be corrected by potassium supplementation in advance of or during use of milrinone.

Drug Interactions

No untoward clinical manifestations have been observed in limited experience with patients in whom milrinone was used concurrently with the following drugs: digitalis glycosides; lidocaine, quinidine; hydralazine, prazosin; isosorbide dinitrate, nitroglycerin; chlorthalidone, furosemide, hydrochlorothiazide, spironolactone; captopril; heparin, warfarin, diazepam, insulin; and potassium supplements.

Chemical Interactions

There is an immediate chemical interaction which is evidenced by the formation of a precipitate when furosemide is injected into an intravenous line of an infusion of milrinone. Therefore, furosemide should not be administered in intravenous lines containing milrinone.

Carcinogenesis, Mutagenesis, Impairment of Fertility

Twenty-four months of oral administration of milrinone to mice at doses up to 40 mg/kg/day (about 50 times the human oral therapeutic dose in a 50 kg patient) was unassociated with evidence of carcinogenic potential. Neither was there evidence of carcinogenic potential when milrinone was orally administered to rats at doses up to 5 mg/kg/day (about 6 times the human oral therapeutic dose) for twenty-four months or at 25 mg/ kg/day (about 30 times the human oral therapeutic dose) for up to 18 months in males and 20 months in females. Whereas the Chinese Hamster Ovary Chromosome Aberration Assay was positive in the presence of a metabolic activation system, results from the Ames Test, the Mouse Lymphoma Assay, the Micronucleus Test, and the in vivo Rat Bone Marrow Metaphase Analysis indicated an absence of mutagenic potential. In reproductive performance studies in rats, milrinone had no effect on male or female fertility at oral doses up to 32 mg/kg/day.

Animal Toxicity

Oral and intravenous administration of toxic dosages of milrinone to rats and dogs resulted in myocardial degeneration/fibrosis and endocardial hemorrhage, principally affecting the left ventricular papillary muscles. Coronary vascular lesions characterized by periarterial edema and inflammation have been observed in dogs only. The myocardial/endocardial changes are similar to those produced by beta-adrenergic receptor agonists such as isoproterenol, while the vascular changes are similar to those produced by minoxidil and hydralazine. Doses within the recommended clinical dose range (up to 1.13 mg/kg/day) for congestive heart failure patients have not produced significant adverse effects in animals.

Pregnancy

Oral administration of milrinone to pregnant rats and rabbits during organogenesis produced no evidence of teratogenicity at dose levels up to 40 mg/kg/day and 12 mg/kg/day, respectively. Milrinone did not appear to be teratogenic when administered intravenously to pregnant rats at doses up to 3 mg/kg/day (about 2.5 times the maximum recommended clinical intravenous dose) or pregnant rabbits at doses up to 12 mg/kg/ day, although an increased resorption rate was apparent at both 8 mg/kg/day and 12 mg/kg/day (intravenous) in the latter species. There are no adequate and well-controlled studies in pregnant women. Milrinone should be used during pregnancy only if the potential benefit justifies the potential risk to the fetus.

Nursing Mothers

Caution should be exercised when milrinone is administered to nursing women, since it is not known whether it is excreted in human milk.

Pediatric Use

Safety and effectiveness in pediatric patients have not been established.

Use in Elderly Patients

There are no special dosage recommendations for the elderly patient. Ninety percent of all patients administered milrinone in clinical studies were within the age range of 45 to 70 years, with a mean age of 61 years. Patients in all age groups demonstrated clinically and statistically significant responses. No age-related effects on the incidence of adverse reactions have been observed. Controlled pharmacokinetic studies have not disclosed any age-related effects on the distribution and elimination of milrinone.

ADVERSE REACTIONS

Cardiovascular Effects

In patients receiving milrinone in Phase II and III clinical trials, ventricular arrhythmias were reported in 12.1%: Ventricular ectopic activity, 8.5%; nonsustained ventricular tachycardia, 2.8%; sustained ventricular tachycardia, 1% and ventricular fibrillation, 0.2% (2 patients experienced more than one type of arrhythmia). Holter recordings demonstrated that in some patients injection of milrinone increased ventricular ectopy, including nonsustained ventricular tachycardia. Life-threatening arrhythmias were infrequent and when present have been associated with certain underlying factors such as preexisting arrhythmias, metabolic abnormalities (e.g. hypokalemia), abnormal digoxin levels and catheter insertion. Milrinone was not shown to be arrhythmogenic in an electrophysiology study. Supraventricular arrhythmias were reported in 3.8% of the patients receiving milrinone. The incidence of both supraventricular and ventricular arrhythmias has not been related to the dose or plasma milrinone concentration.

Other cardiovascular adverse reactions include hypotension, 2.9% and angina/chest pain, 1.2%.

In the post marketing experience, there have been rare cases of “torsades de pointes” reported.

CNS Effects
Headaches, usually mild to moderate in severity, have been reported in 2.9% of patients receiving milrinone.

Other Effects
Other adverse reactions reported, but not definitely related to the administration of milrinone include hypokalemia, 0.6%; tremor, 0.4%; and thrombocytopenia, 0.4%.

Post-Marketing Adverse Event Reports
In addition to adverse events reported from clinical trials, the following events have been reported from worldwide post-marketing experience with Milrinone:
Isolated spontaneous reports of bronchospasm and anaphylactic shock.
Liver function test abnormalities and skin reactions such as rash.
Administration site conditions: Infusion site reaction.

OVERDOSAGE

Doses of milrinone may produce hypotension because of its vasodilator effect. If this occurs, administration of milrinone should be reduced or temporarily discontinued until the patient’s condition stabilizes. No specific antidote is known, but general measures for circulatory support should be taken.

DOSAGE AND ADMINISTRATION

Milrinone Lactate in 5% Dextrose Injection should be administered with a loading dose followed by a continuous infusion (maintenance dose) according to the following guidelines:
Loading Dose
50 mcg/kg: Administer slowly over 10 minutes
Note: Milrinone (200 mcg per mL) in Plastic Container is for intravenous infusion only.
Dosage recommendations using a 1 mg per mL concentration of milrinone are included for informational purposes only.

The table below shows the loading dose in milliliters (mL) of milrinone (1 mg/mL) by patient body weight (kg).

Loading Dose (mL) Using 1 mg/mL Concentration

Patient Body Weight (kg)
kg | 30 | 40 | 50 | 60 | 70 | 80 | 90 | 100 | 110 | 120
mL | 1.5 | 2.0 | 2.5 | 3.0 | 3.5 | 4.0 | 4.5 | 5.0 | 5.5 | 6.0

The loading dose may be given undiluted, but diluting to a rounded total volume of 10 or 20 mL (see Maintenance Dose for diluents) may simplify the visualization of the injection rate.

Maintenance Dose

 | Infusion Rate | Total Daily Dose (24 Hours)
Minimum Standard Maximum | 0.375 mcg/kg/min 0.50 mcg/kg/min 0.75 mcg/kg/min | 0.59 mg/kg 0.77 mg/kg 1.13 mg/kg | Administer as a continuous intravenous infusion

The infusion rate should be adjusted according to hemodynamic and clinical response. Patients should be closely monitored. In controlled clinical studies, most patients showed an improvement in hemodynamic status as evidenced by increases in cardiac output and reductions in pulmonary capillary wedge pressure.
Note: See “Dosage Adjustment in Renally Impaired Patients.” Dosage may be titrated to the maximum hemodynamic effect and should not exceed 1.13 mg/kg/day. Duration of therapy should depend upon patient responsiveness.
The maintenance dose in mL/hr by patient body weight (kg) may be determined by reference to the following table.

Milrinone Infusion Rate (mL/hr) Using 200 mcg/mL Concentration

Maintenance Dose (mcg/kg/min) | Patient Body Weight (kg)
Maintenance Dose (mcg/kg/min) | 30 | 40 | 50 | 60 | 70 | 80 | 90 | 100 | 110 | 120
0.375 | 3.4 | 4.5 | 5.6 | 6.8 | 7.9 | 9.0 | 10.1 | 11.3 | 12.4 | 13.5
0.400 | 3.6 | 4.8 | 6.0 | 7.2 | 8.4 | 9.6 | 10.8 | 12.0 | 13.2 | 14.4
0.500 | 4.5 | 6.0 | 7.5 | 9.0 | 10.5 | 12.0 | 13.5 | 15.0 | 16.5 | 18.0
0.600 | 5.4 | 7.2 | 9.0 | 10.8 | 12.6 | 14.4 | 16.2 | 18.0 | 19.8 | 21.6
0.700 | 6.3 | 8.4 | 10.5 | 12.6 | 14.7 | 16.8 | 18.9 | 21.0 | 23.1 | 25.2
0.750 | 6.8 | 9.0 | 11.3 | 13.5 | 15.8 | 18.0 | 20.3 | 22.5 | 24.8 | 27.0

Dosage Adjustment in Renally Impaired Patients
Data obtained from patients with severe renal impairment (creatinine clearance = 0 to 30 mL/min) but without congestive heart failure have demonstrated that the presence of renal impairment significantly increases the terminal elimination half-life of milrinone. Reductions in infusion rate may be necessary in patients with renal impairment. For patients with clinical evidence of renal impairment, the recommended infusion rate can be obtained from the following table:

Creatinine Clearance (mL/min/1.73m^2) | Infusion Rate (mcg/kg/min)
5 | 0.20
10 | 0.23
20 | 0.28
30 | 0.33
40 | 0.38
50 | 0.43

Parenteral drug products should be inspected visually for particulate matter and discoloration prior to administration, whenever solution and container permit. Milrinone Lactate in 5% Dextrose Injection is a clear, colorless to pale yellow solution.

DIRECTIONS FOR USE

When administering Milrinone Lactate in 5% Dextrose Injection by continuous infusion, it is advisable to use a calibrated electronic infusion device.
To open
Tear at the notch and open the overwrap to remove solution container. Some opacity of the plastic due to moisture absorption during the sterilization process may be observed. This is normal and does not affect the solution quality or safety. The opacity will diminish gradually. After removing overwrap, check for minute leaks by squeezing inner bag firmly. If leaks are found, discard solution as sterility may be impaired.
Preparation for Administration
Visually inspect the container. If the administration port is damaged, detached, or not present, discard container as solution path sterility may be impaired.
(Use aseptic technique)
1. Suspend container from eyelet support.
2. Remove top portion of twist off port at bottom of container.
3. Attach administration set. Refer to complete directions accompanying set.

WARNING: DO NOT USE IN SERIES CONNECTIONS. Do not administer simultaneously with blood. Caution: Do not use plastic containers in series connections. Such use could result in air embolism due to residual air being drawn from the primary container before administration of the fluid from the secondary container is complete.

HOW SUPPLIED

Milrinone Lactate in 5% Dextrose Injection is a clear, colorless to pale yellow solution and is supplied in Infusion bags as follows:

NDC No. | Milrinone Lactate in 5% Dextrose Injection (200 mcg (0.2 mg) per mL) | Pack Style
65145-176-01 | 20 mg per 100 mL Single-Dose Infusion bag | 1 Single-dose Infusion Bag in an Overwrap
65145-177-01 | 40 mg per 200 mL Single-Dose Infusion bag | 1 Single-dose Infusion Bag in an Overwrap

Exposure of pharmaceutical products to heat should be minimized. Avoid excessive heat. Protect from freezing. It is recommended that the Flexible Containers be stored at room temperature, 25°C (77°F), however, brief exposure up to 40°C (104°F) does not adversely affect the product.

Discard unused portion.

Made in India
Distributed By :
Caplin Steriles USA Inc,
Hamilton, NJ 08619.
Code: TN/Drugs/TN00003462
Code: TN/Drugs/TN00006405

July, 2025

22201142

PACKAGE LABEL.PRINCIPAL DISPLAY PANEL

20 mg per 100 mL Bag Label
NDC 65145-176-01

100 mL Single-Dose Flexible Container
Milrinone Lactate
in 5% Dextrose Injection
20 mg/100 mL

200 mcg (0.2 mg) per mL

20 mg per 100 mL Pouch Label
NDC 65145-176-01

100 mL Single-Dose Flexible Container
Milrinone Lactate
in 5% Dextrose Injection
20 mg/100 mL

200 mcg (0.2 mg) per mL

40 mg per 200 mL Bag Label
NDC 65145-177-01

200 mL Single-Dose Flexible Container
Milrinone Lactate
in 5% Dextrose Injection
40 mg/200 mL

200 mcg (0.2 mg) per mL

40 mg per 200 mL Pouch Label

NDC 65145-177-01

200 mL Single-Dose Flexible Container
Milrinone Lactate
in 5% Dextrose Injection
40 mg/200 mL

200 mcg (0.2 mg) per mL